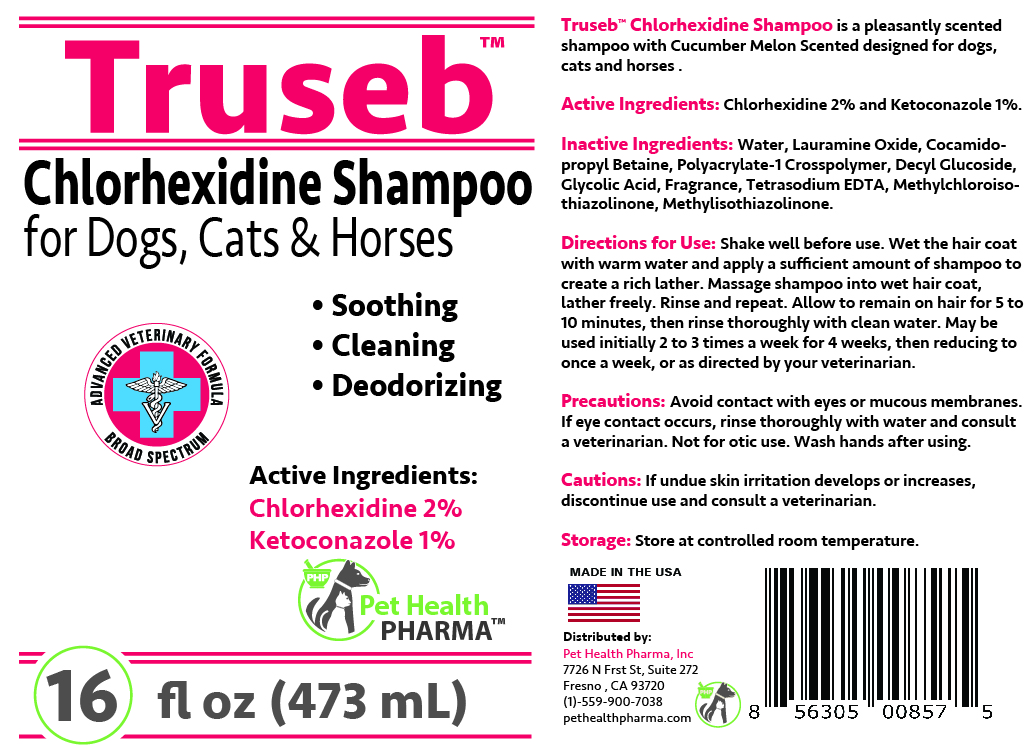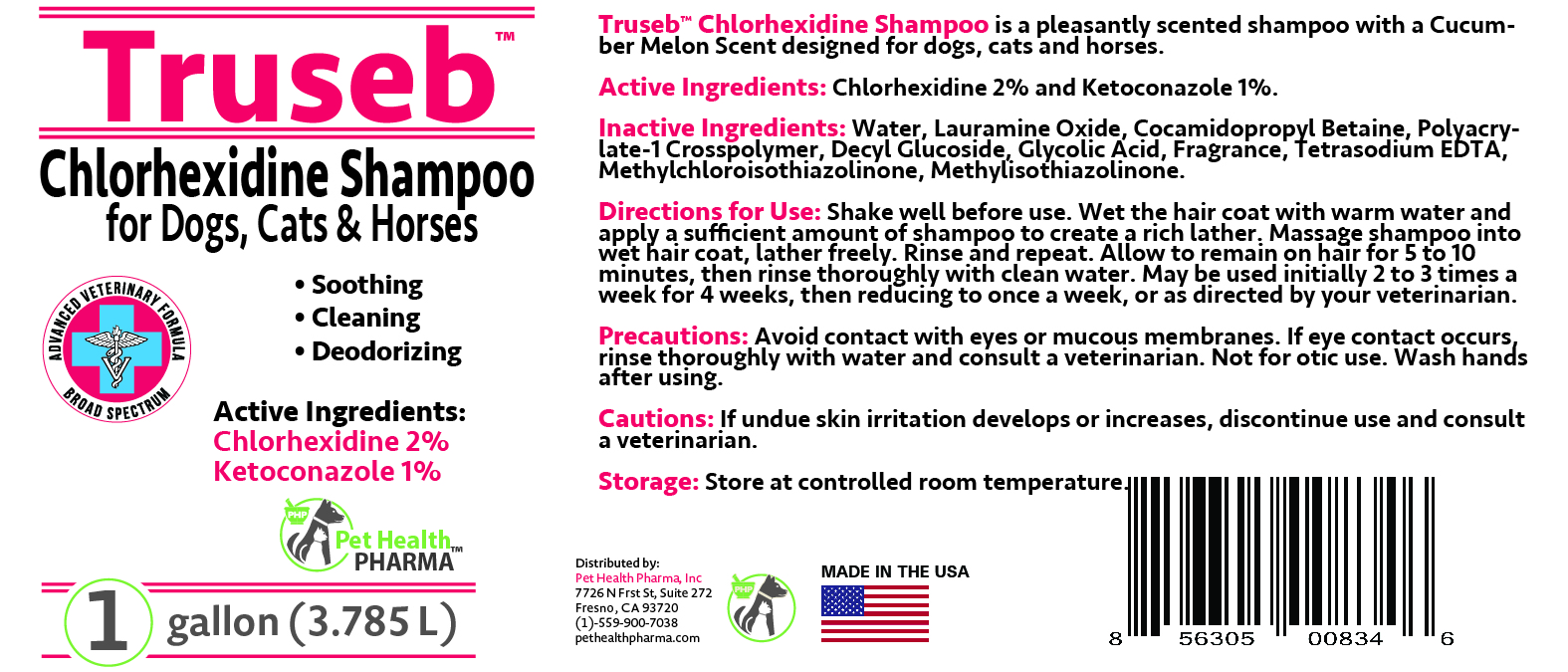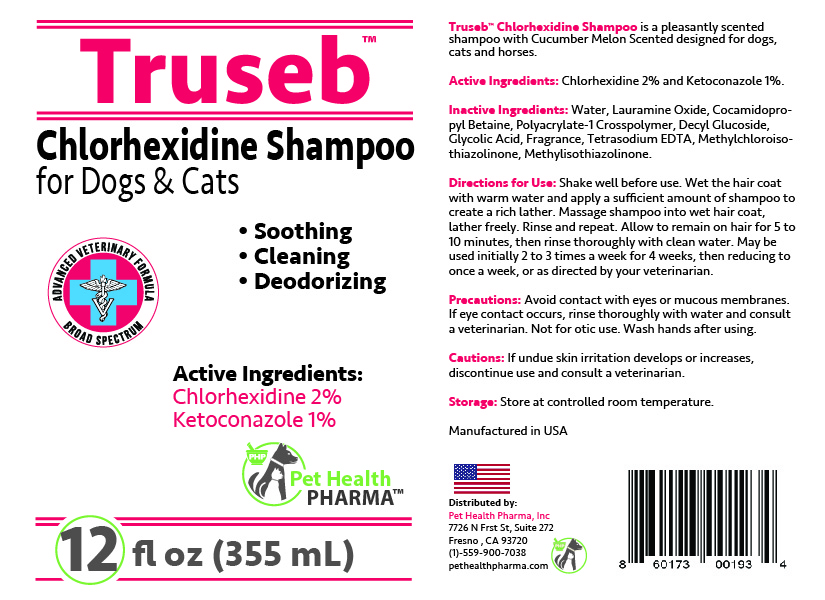 DRUG LABEL: TRUSEB CHLORHEXIDINE GLUCONATE, KETOCONAZOLE FOR DOGS, CATS AND HORSES
NDC: 86176-207 | Form: SHAMPOO
Manufacturer: Pet Health Pharma, LLC
Category: animal | Type: OTC ANIMAL DRUG LABEL
Date: 20250213

ACTIVE INGREDIENTS: CHLORHEXIDINE GLUCONATE 2 g/100 mL; KETOCONAZOLE 1 g/100 mL
INACTIVE INGREDIENTS: WATER; LAURAMINE OXIDE; COCAMIDOPROPYL BETAINE; POLYACRYLATE-1 CROSSPOLYMER; DECYL GLUCOSIDE; GLYCOLIC ACID; TETRASODIUM EDTA; METHYLCHLOROISOTHIAZOLINONE; METHYLISOTHIAZOLINONE

Truseb Chlorhexidine, Ketoconazole Shampoo For Cats, Dogs and Horses

ACTIVE INGREDIENT:

Chlorhexidine Gluconate 2% and Ketoconazole 1%.

INACTIVE INGREDIENTS:

Water, Lauramine Oxide, Cocamidopropyl Betaine, Polyacrylate-1 Crosspolymer, Decyl Glucoside, Glycolic Acid, Fragrance, Tetrasodium EDTA, Methylchloroisothiazolinone, Methylisothiazolinone.

INDICATIONS & USAGE:

Truseb™ Chlorhexidine Shampoo is a pleasantly scented shampoo with Cucumber Melon Scented designed for dogs, cats and horses

DIRECTIONS FOR USE:

Shake well before use. Wet the hair coat with warm water and apply a sufficient amount of shampoo to create a rich lather. Massage shampoo into wet hair coat, lather freely. Allow to remain on hair for 5 to 10 minutes, then rinse thoroughly with clean water and repeat. May be used initially 2 to 3 times a week for 4 weeks, then reducing to once a week, or as directed by your veterinarian.

PRECAUTIONS:

Avoid contact with eyes or mucous membranes. If eye contact occurs, rinse thoroughly with water and consult a veterinarian. Not for otic use. Wash hands after using

Cautions:

If undue skin irritation develops or increases, discontinue use and consult a veterinarian.

STORAGE:

Store at controlled room temperature.

SPL UNCLASSIFIED SECTION

Chlorhexidine Shampoo
For Dogs, Cats & Horses

- Soothing
- Cleaning
- Deodorizing

ADVANCED VETERINARY FORMULA
Broad Spectrum
Manufactured in USA

Distributed by:
Pet Health Pharma, Inc
7726 N Frst St, Suite 272
Fresno , CA 93720
(1)-559-900-7038
pethealthpharma.com

PACKAGE LABEL

Packaging

Add image transcription here...

Add image transcription here...

Add image transcription here...